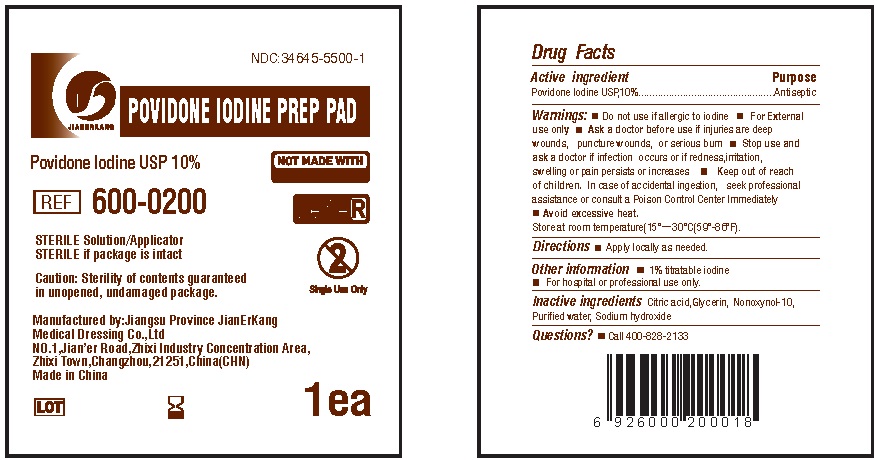 DRUG LABEL: Povidone Iodine Prep Pad
NDC: 34645-5500 | Form: SOLUTION
Manufacturer: Jianerkang Medical Co., Ltd
Category: otc | Type: HUMAN OTC DRUG LABEL
Date: 20231023

ACTIVE INGREDIENTS: POVIDONE-IODINE 10 g/100 g
INACTIVE INGREDIENTS: CITRIC ACID MONOHYDRATE; GLYCERIN; NONOXYNOL-10; WATER; SODIUM HYDROXIDE

Povidone Iodine Prep Pad

Active ingredient

Povidone lodine USP,10% w/v (equivalent to 1% titratable iodine)

PURPOSE

First Aid Antiseptic

Use

First aid to help prevent infection in minor cuts,scrqpes,and burns

Warnings

For external use only.

Do not

- use in the eyes
- apply over large areas of the body.
- use on individuals who are allergic or sensitive to iodine.

Stop use and consult a doctor

- if the condition persists or gets worse
- for use longer than 1 week.

Ask a doctor

in case of deep or puncture wounds, animal bites,serious burns.

Keep out of reach of children.

if swallowed, get medical help or contact a Poison Control Center right away.

Directions

- Clean the affected area
- Apply product on the area 1-3 times daily and discard
- May be covered with a sterile bandage when dry

Other information

- Avoid excessive heat
- store at room temperature: 15°－30°C(59°-86°F)

Inactive ingredients

citric acid,glycerin Nonoxynol-10, purified water, sodium hydroxide